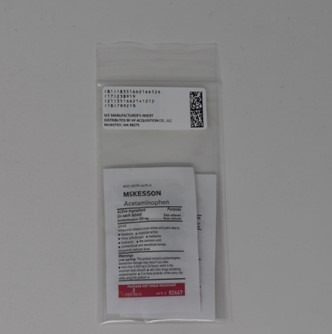 DRUG LABEL: acetaminophen
NDC: 51662-1665 | Form: TABLET, COATED
Manufacturer: HF Acquisition Co LLC, DBA HealthFirst
Category: otc | Type: HUMAN OTC DRUG LABEL
Date: 20260115

ACTIVE INGREDIENTS: ACETAMINOPHEN 325 mg/1 1
INACTIVE INGREDIENTS: HYPROMELLOSE, UNSPECIFIED; POLYETHYLENE GLYCOL, UNSPECIFIED; SODIUM STARCH GLYCOLATE TYPE A POTATO; STEARIC ACID; POVIDONE, UNSPECIFIED; STARCH, CORN; TITANIUM DIOXIDE

Active ingredient (in each tablet)

Acetaminophen 325 mg

PURPOSE

Pain reliever/fever reducer

INDICATIONS AND USAGE

temporarily relieves of minor aches and pains due to:

■ headache

■ muscular aches

■ minor arthritis pain

■ backache

■ the common cold

■ toothache

■ premenstrual and menstrual cramps

■ temporarily reduces fever

WARNINGS

Liver warning: This product contains acetaminophen. Severe liver damage may occur if you take:

■ more than 4,000 mg in 24 hours, which is the maximum daily amount

■ with other drugs containing acetaminophen

■ 3 or more alcoholic drinks every day while using this product

Allergy alert: Acetaminophen may cause severe skin reactions. Symptoms may include:

■ skin reddening

■ blisters

■ rash

If a skin reaction occurs, stop use and seek medical help right away.

DO NOT USE

■ with any other drug containing acetaminophen (prescription or nonprescription). If you are not sure whether a
drug contains acetaminophen, ask a doctor or pharmacist.

■ if you are allergic to acetaminophen or any of the inactive ingredients in this product

Ask a doctor before use if you have

■ liver disease

Ask a doctor or pharmacist before use if

■ you are taking the blood thinning drug warfarin

Stop using and ask a doctor if

■ pain gets worse and lasts for more than 10 days

■ fever gets worse or lasts for more than 3 days

■ new symptoms occur

■ redness or swelling is present

These could be signs of a serious condition

Keep out of reach of children.

Directions

■ do not use more than directed (see overdose warning)

Adults and children: (12 years and over)

■ take 2 tablets every 4 to 6 hours while symptoms last.

■ do not take more than 10 tablets in 24 hours, unless directed by a doctor

■ do not use for more than 10 days unless directed by a doctor

Children under 12 years:

■ Ask a doctor

INACTIVE INGREDIENT

corn starch, hypromellose, polyethylene glycol, povidne, pregelantinized starch, sodium starch glycolate, stearic acid, titanium dioxide

OVERDOSAGE

Overdose Warning:

In case of overdose, get medical help or contact a Poison Control Center right away (1-800-222-1222). Quick medical attention is critical for adults as well as for children even if you do not notice any signs or symptoms.

STORAGE AND HANDLING

■ store at room temperature 59º-86ºF (15º-30ºC)

■ tamper-evident sealed packets

■ do not use any opened or torn packets

HOW SUPPLIED

2 in 1 packet; 1 packet in 1 pouch.